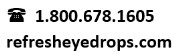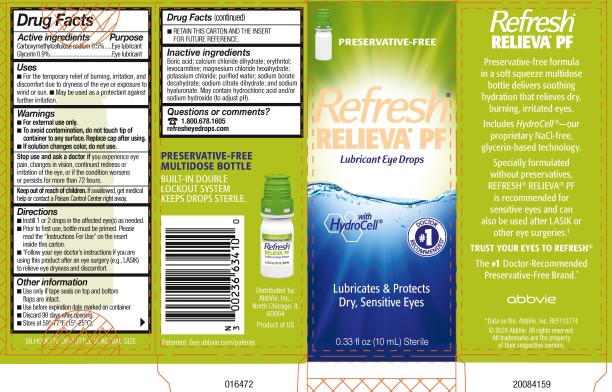 DRUG LABEL: Refresh Relieva Preservative Free
NDC: 0023-6634 | Form: SOLUTION/ DROPS
Manufacturer: Allergan, Inc.
Category: otc | Type: HUMAN OTC DRUG LABEL
Date: 20251022

ACTIVE INGREDIENTS: CARBOXYMETHYLCELLULOSE SODIUM 5 mg/1 mL; GLYCERIN 9 mg/1 mL
INACTIVE INGREDIENTS: BORIC ACID; CALCIUM CHLORIDE; ERYTHRITOL; LEVOCARNITINE; MAGNESIUM CHLORIDE; POTASSIUM CHLORIDE; WATER; SODIUM BORATE; TRISODIUM CITRATE DIHYDRATE; HYALURONATE SODIUM; HYDROCHLORIC ACID; SODIUM HYDROXIDE

REFRESH RELIEVA PF®
Drug Facts

Active ingredients

Carboxymethylcellulose sodium 0.5%
Glycerin 0.9%

Purpose

Eye lubricant
Eye lubricant

Uses

- For the temporary relief of burning, irritation, and discomfort due to dryness of the eye or exposure to wind or sun.
- May be used as a protectant against further irritation.

Warnings

- For external use only.
- To avoid contamination, do not touch tip of container to any surface. Replace cap after using.
- If solution changes color or becomes cloudy, do not use.

Stop use and ask a doctor if

you experience eye pain, changes in vision, continued redness or irritation of the eye, or if the condition worsens or persists for more than 72 hours.

Keep out of reach of children.

If swallowed, get medical help or contact a Poison Control Center right away.

Directions

- Instill 1 or 2 drops in the affected eye(s) as needed.
- Prior to first use, bottle must be primed. Please read the “Instructions For Use” on the insert inside this carton.
- *Follow your eye doctor’s instructions if you are using this product after an eye surgery (e.g., LASIK) to relieve eye dryness and discomfort.

Other information

- Use only if tape seals on top and bottom flaps are intact.
- Use before expiration date marked on container.
- Discard 90 days after opening.
- Store at 59°-77°F (15°-25°C).
- RETAIN THIS CARTON AND THE INSERT FOR FUTURE REFERENCE.

Inactive ingredients

Boric acid; calcium chloride dihydrate; erythritol; levocarnitine; magnesium chloride hexahydrate; potassium chloride; purified water; sodium borate decahydrate; sodium citrate dihydrate; and sodium hyaluronate. May contain hydrochloric acid and/or sodium hydroxide (to adjust pH).

Questions or comments?

v2.0DFL6634

PRINCIPAL DISPLAY PANEL

NDC: 0023-6634-10

PRESERVATIVE-FREE
Refresh®
RELIEVA® PF
Lubricant Eye Drops
With Hydrocell®
Lubricates &Protects
Dry,Sensitive Eyes
0.33 fl oz (10 mL) Sterile